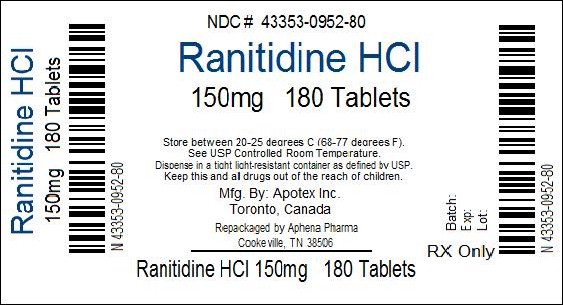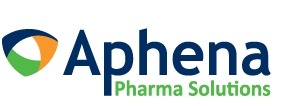 DRUG LABEL: Ranitidine
NDC: 43353-952 | Form: TABLET, FILM COATED
Manufacturer: Aphena Pharma Solutions - Tennessee, LLC
Category: otc | Type: HUMAN OTC DRUG LABEL
Date: 20160601

ACTIVE INGREDIENTS: Ranitidine Hydrochloride 150 mg/1 1
INACTIVE INGREDIENTS: Carnauba Wax; Silicon Dioxide; Hypromelloses; Magnesium Stearate; Cellulose, Microcrystalline; Polydextrose; Titanium Dioxide; Vanillin; Ferric Oxide Red; Ferric Oxide Yellow

Drug Facts

Active ingredient (in each tablet)

Ranitidine 150 mg (as ranitidine hydrochloride, USP 168 mg)

Purpose

Acid reducer

Uses

- relieves heartburn associated with acid indigestion and sour stomach
- prevents heartburn associated with acid indigestion and sour stomach brought on by eating or drinking certain foods and beverages

Warnings

Allergy alert: Do not use if you are allergic to ranitidine or any other acid reducers

Do not use

- if you have trouble or pain swallowing food, vomiting with blood, or bloody or black stools. These may be signs of a serious condition. See your doctor.
- with other acid reducers
- if you have kidney disease, except under the advice and supervision of a doctor

Ask a doctor before use if you have

- had heartburn over 3 months. This may be a sign of a more serious condition.
- heartburn with lightheadedness, sweating or dizziness
- chest pain or shoulder pain with shortness of breath; sweating; pain spreading to arms, neck or shoulders; or lightheadedness
- frequent chest pain
- frequent wheezing, particularly with heartburn
- unexplained weight loss
- nausea or vomiting
- stomach pain

Stop use and ask a doctor if

- your heartburn continues or worsens
- you need to take this product for more than 14 days

PREGNANCY OR BREAST FEEDING

If pregnant or breast-feeding, ask a health professional before use.

Keep out of reach of children.

In case of overdose, get medical help or contact a Poison Control Center right away.

Directions

- adults and children 12 years and over:
  - to relieve symptoms, swallow 1 tablet with a glass of water
  - to prevent symptoms, swallow 1 tablet with a glass of water 30 to 60 minutes before eating food or drinking beverages that cause heartburn
  - can be used up to twice daily (do not take more than 2 tablets in 24 hours)
- children under 12 years: ask a doctor

Other information

- do not use if printed foil under bottle cap is broken or torn
- store at 20°C to 25°C (68°F to 77°F)
- avoid excessive heat or humidity
- this product is sodium and sugar free

Inactive ingredients

carnauba wax, colloidal silicon dioxide, ferric oxide red, ferric oxide yellow, hypromellose, magnesium stearate, microcrystalline cellulose, polyethylene glycol, titanium dioxide and vanillin

Questions or Comments?

Call 1-800-706-5575 (Monday to Friday 8:30 a.m. – 5:00 p.m. Eastern Standard Time)

Repackaging Information

Please reference the How Supplied section listed above for a description of individual tablets. This drug product has been received by Aphena Pharma - TN in a manufacturer or distributor packaged configuration and repackaged in full compliance with all applicable cGMP regulations. The package configurations available from Aphena are listed below:

Count | 150mg
180 | 43353-952-80
1000 | 43353-952-71

Store between 20°-25°C (68°-77°F). See USP Controlled Room Temperature. Dispense in a tight light-resistant container as defined by USP. Keep this and all drugs out of the reach of children.

Repackaged by:
Cookeville, TN 38506
20160602DH

Principal Display Panel

Maximum Strength

Ranitidine Tablets USP, 150 mg 180 & 1000 ct bottle

Acid Reducer

Prevents & Relieves

Heartburn Associated with Acid Indigestion & Sour Stomach

Distributed by: Apotex Corp. Weston, Florida 33326, USA.

PRINCIPAL DISPLAY PANEL - 150mg

NDC 43353-952 - Ranitidine HCl 150mg - Rx Only